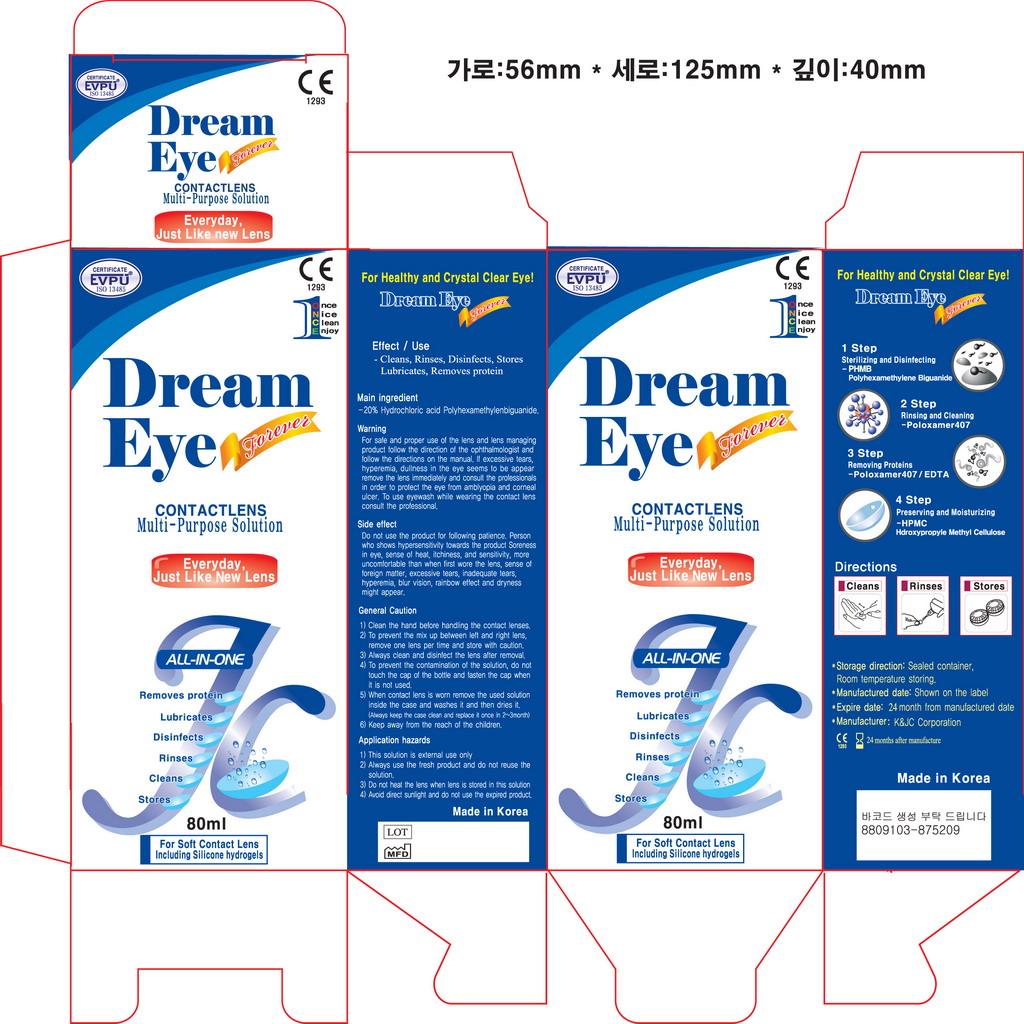 DRUG LABEL: Dream Eye
NDC: 52345-3001 | Form: LIQUID
Manufacturer: K&J.C Co., Ltd
Category: otc | Type: HUMAN OTC DRUG LABEL
Date: 20101013

ACTIVE INGREDIENTS: POLOXAMER 407 0.1 mL/1 mL
INACTIVE INGREDIENTS: SODIUM CHLORIDE; SODIUM BORATE; BORIC ACID; HYPROMELLOSES; EDETATE DISODIUM; WATER

Drug Facts

Active Ingredient: Poloxamer 407

DESCRIPTION

STEP 1:
Place 3 drops of Dream Eye on each side of contact lens and rub for 20 seconds. No
necessary. separate daily cleaner
STEP 2:
Remove surface debris by rinsing thoroughly with Dream Eye
STEP 3:
Place cleaned contact lens in the lens case and fill with fresh Dream Eye MPS. Soak at
least four(4) hours.

WHEN USING

Cleans, loosens and removes accumulations of film, deposits and debris from
soft contact lenses. Destroys harmful micro-organisms on the surface of the
lens. Rinse, stores and rewets lenses before insertion. For dissolving of
Enzymatic Contact Lens Cleaner tablets for removal of protein deposits.

PRECAUTIONS:
☞ Never re-use this solution.
☞ Keep the bottle tightly closed when not in use.
☞ Store at room temperature.
☞ Use before the expiration date marked on the bottle and carton.

PURPOSE

ACTIONS: Cleans, loosens and removes accumulations of film, deposits and debris from
soft contact lenses. Destroys harmful micro-organisms on the surface of the
lens. Rinse, stores and rewets lenses before insertion. For dissolving of
Enzymatic Contact Lens Cleaner tablets for removal of protein deposits.

Keep out of the reach of children

INDICATIONS AND USAGE

INDICATIONS(Uses): Dream Eye is indicated for use in daily cleaning,
dissolving of Enzymatic Contact Lens Cleaner tablets, rinsing and storage of daily
and extended wear soft contact lenses and chemical (not heat)
disinfection, as recommended by your eye care professional.

WARNINGS

WARNING: PROBLEMS WITH CONTACT LENSES AND LENS CARE PRODUCTS COULD
RESULT IN SERIOUS INJURY TO THE EYE. It is essential that you follow your
eye care practitioner's directions and all labeling instructions for proper use
and care of your lenses and lens care products, including the lens case.
☞ To avoid contamination, do not touch tip of container to any surface. Replace cap
after using.
☞ Not intended for use directly in the eye.
☞ Not for use with heat(thermal) disinfection.

DIRECTIONS:
☞ After removing the lens, place it in the palm of your hand, and place three drops of
Daily Cleaner on each lens surface. or Soak at least four(4) hours in Dream Eye.
☞ Rub the lens for 20 seconds either in the palm of your hand using the forefinger
of the other hand, or between the thumb and forefinger. Be sure to clean each side
of the lens.
☞ Rinse the lens thoroughly by holding the lens in a steady stream of saline solution
for approximately 10 seconds.
☞ Disinfect using the procedure which your practitioner has recommended.

Inactive ingredient: Sodium Chloride, Sodium Borate, Boric Acid, HYPROMELLOSES, EDETATE DISODIUM, Water